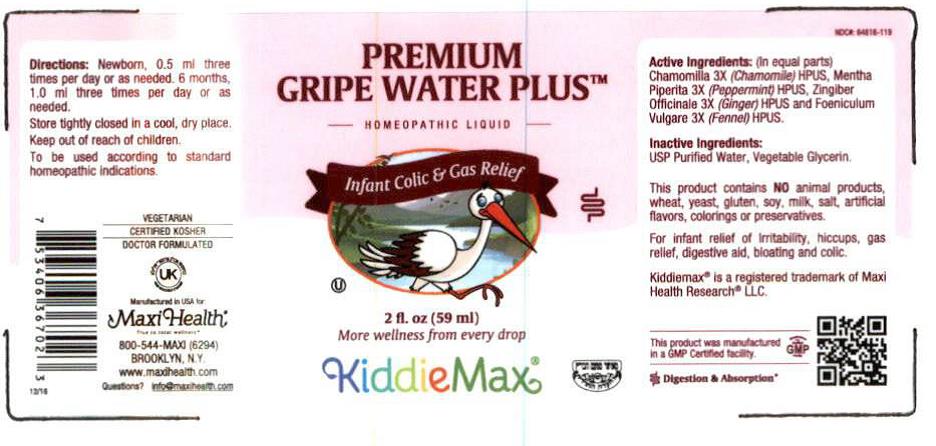 DRUG LABEL: Gripe Water
NDC: 64616-119 | Form: LIQUID
Manufacturer: Vitality Works
Category: homeopathic | Type: HUMAN OTC DRUG LABEL
Date: 20251217

ACTIVE INGREDIENTS: MATRICARIA CHAMOMILLA WHOLE 1 [hp_X]/0.0025 mL; MENTHA PIPERITA 1 [hp_X]/0.0025 mL; ZINGIBER OFFICINALE WHOLE 1 [hp_X]/0.0025 mL; FOENICULUM VULGARE VAR. VULGARE WHOLE 1 [hp_X]/0.0025 mL
INACTIVE INGREDIENTS: GLYCERIN; WATER

Maxi-Health Gripe water

Active Ingredients

(In equal parts) Chamomila 3x (Chamomile) HPUS, Mentha Piperita 3x (Peppermint) HPUS, Zingaber Officianale 3x (Ginger) HPUS, and Foeniculum Vulgare 3x (Fennel) HPUS.

Inactive Ingredients:

USP Purified Water, Vegetable Glycerin

Keep out of reach of children

Directions:

Newborn, 0.5 ml tthree times per day or as needed. 6 months, 1.0 ml three times per day or as needed.

To be used according to standard homepoathic indications

PURPOSE

For infant relief of irritiability, hiccups, gas releif, digestive aid, bloating and colic.

Questions

info@maxihealth.com

WARNINGS

Store tightly in a cool dry place. Keep out of reach of childre,To be used according to standard homeopathic indications.

INDICATIONS AND USAGE

For relief of irritability, hiccips, gas relief, digestive aid, bloating and colic